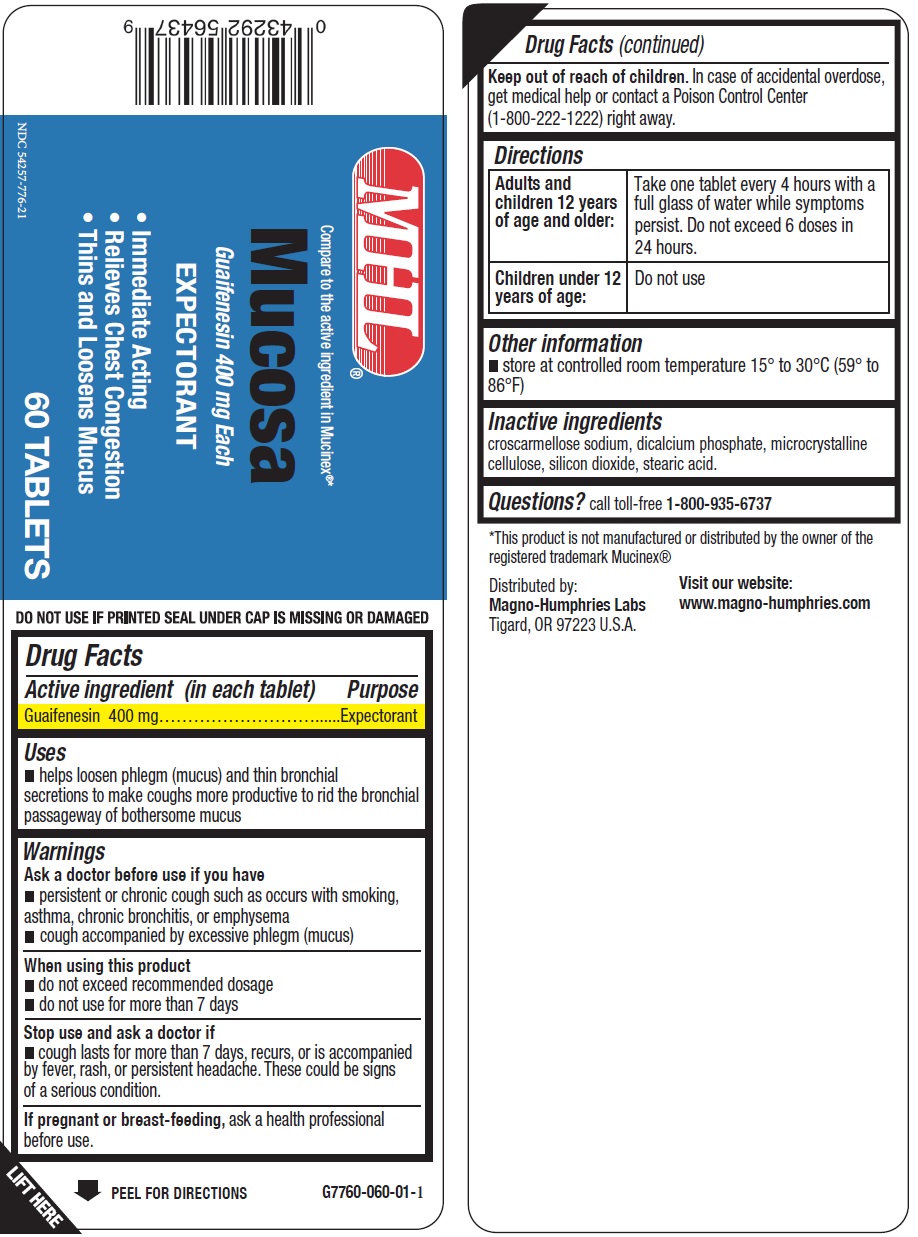 DRUG LABEL: Mucosa Guifenesin
NDC: 54257-776 | Form: TABLET
Manufacturer: Magno-Humphries, Inc.
Category: otc | Type: HUMAN OTC DRUG LABEL
Date: 20231027

ACTIVE INGREDIENTS: GUAIFENESIN 400 mg/1 1
INACTIVE INGREDIENTS: CROSCARMELLOSE SODIUM; ANHYDROUS DIBASIC CALCIUM PHOSPHATE; MICROCRYSTALLINE CELLULOSE; SILICON DIOXIDE; STEARIC ACID

Mucosa Guifenesin

Active ingredient (in each tablet)

Guaifenesin 400 mg

Purpose

Expectorant

Uses

- helps loosen phlegm (mucus) and thin bronchial secretions to make coughs more productive to rid the bronchial passageway of bothersome mucus

Warnings

Ask a doctor before use if you have

- persistent or chronic cough such as occurs with smoking, asthma, chronic bronchitis, or emphysema
- cough accompanied by excessive phlegm (mucus)

When using this product

- do not exceed recommended dosage
- do not use for more than 7 days

Stop use and ask a doctor if

- cough lasts for more than 7 days, recurs, or is accompanied by fever, rash, or persistent headache. These could be signs of a serious condition.

If pregnant or breast-feeding,

ask a health professional before use.

Keep out of reach of children.

In case of accidental overdose, get medical help or contact a Poison Control Center (1-800-222-1222) right away.

Directions

Adults and children 12 years of age and older: | Take one tablet every 4 hours with a full glass of water while symptoms persist. Do not exceed 6 doses in 24 hours.
Children under 12 years of age: | Do not use

Other information

- store at controlled room temperature 15° to 30°C (59° to 86°F)

Inactive ingredients

croscarmellose sodium, dicalcium phosphate, microcrystalline cellulose, silicon dioxide, stearic acid.

Questions?

call toll-free 1-800-935-6737